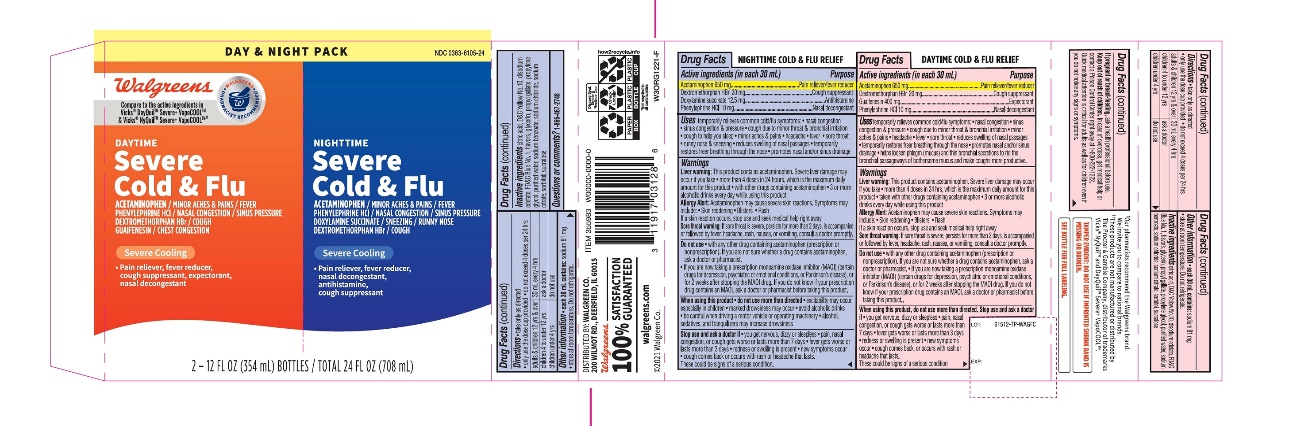 DRUG LABEL: Walgreen Day Time NightTime Cold and Flu Relief
NDC: 0363-6105 | Form: KIT | Route: ORAL
Manufacturer: WALGREENS CO.
Category: otc | Type: HUMAN OTC DRUG LABEL
Date: 20251201

ACTIVE INGREDIENTS: ACETAMINOPHEN 650 mg/30 mL; DEXTROMETHORPHAN HYDROBROMIDE 20 mg/30 mL; DOXYLAMINE SUCCINATE 12.5 mg/30 mL; PHENYLEPHRINE HYDROCHLORIDE 10 mg/30 mL; ACETAMINOPHEN 650 mg/30 mL; DEXTROMETHORPHAN HYDROBROMIDE 20 mg/30 mL; GUAIFENESIN 400 mg/30 mL; PHENYLEPHRINE HYDROCHLORIDE 10 mg/30 mL
INACTIVE INGREDIENTS: ANHYDROUS CITRIC ACID; D&C YELLOW NO. 10; EDETATE DISODIUM; FD&C BLUE NO. 1; GLYCERIN; PROPYL GALLATE; PROPYLENE GLYCOL; WATER; SODIUM BENZOATE; SODIUM CHLORIDE; SODIUM CITRATE, UNSPECIFIED FORM; SORBITOL; SUCRALOSE; ANHYDROUS CITRIC ACID; D&C YELLOW NO. 10; EDETATE DISODIUM; FD&C BLUE NO. 1; GLYCERIN; PROPYL GALLATE; PROPYLENE GLYCOL; WATER; SODIUM BENZOATE; SODIUM CHLORIDE; SODIUM CITRATE, UNSPECIFIED FORM; SORBITOL; SUCRALOSE

Walgreen DayTime NightTime Cold & Flu Drug Facts

Active ingredients (in each 30 mL) – NightTime

Acetaminophen 650 mg

Dextromethorphan HBr 20 mg

Doxylamine succinate 12.5 mg

Phenylephrine HCl 10 mg

Purpose

Pain reliever/fever reducer

Cough suppressant

Antihistamine

Nasal decongestant

Uses

temporarily relieves common cold/flu symptoms:

- nasal congestion
- sinus congestion and pressure
- minor aches and pains
- headache
- fever
- sore throat
- runny nose and sneezing
- cough due to minor throat and bronchial irritation
- cough to help you sleep
- reduces swelling of nasal passages
- promotes nasal and/or sinus drainage
- temporarily restores freer breathing through the nose

Warnings

Liver warning:This product contains acetaminophen. Severe liver damage may occur if you take

- more than 4 doses in 24 hours, which is the maximum daily amount for this product
- with other drugs containing acetaminophen
- 3 or more alcoholic drinks every day while using this product

Allergy alert:Acetaminophen may cause severe skin reactions. Symptoms may include:

- Skin reddening
- Blisters
- Rash

If a skin reaction occurs, stop use and seek medical help right away.

Sore throat warning:If sore throat is severe, persists for more than 2 days, is accompanied or followed by fever, headache, rash, nausea, or vomiting, consult a doctor promptly.

Do not use

- with any other drug containing acetaminophen (prescription or nonprescription). If you are not sure whether a drug contains acetaminophen, ask a doctor or pharmacist.
- if you are now taking a prescription monoamine oxidase inhibitor (MAOI) (certain drugs for depression, psychiatric, or emotional conditions, or Parkinson’s disease), or for 2 weeks after stopping the MAOI drug. If you do not know if your prescription drug contains an MAOI, ask a doctor or pharmacist before taking this product.

When using this product

- do not use more than directed
- excitability may occur, especially in children
- marked drowsiness may occur
- avoid alcoholic drinks
- be careful when driving a motor vehicle or operating machinery
- alcohol, sedatives, and tranquilizers may increase drowsiness

Stop use and ask a doctor if

- you get nervous, dizzy or sleepless
- pain, nasal congestion, or cough gets worse or lasts more than 7 days
- fever gets worse or lasts more than 3 days
- redness or swelling is present
- new symptoms occur
- cough comes back or occurs with rash or headache that lasts. These could be signs of a serious condition.

Directions

- take only as directed – see Overdose warning
- only use the dose cup provided
- do not exceed 4 doses per 24 hrs

adults & children 12 yrs & over | 30 mL every 4 hrs
children 4 to under 12 yrs | ask a doctor
children under 4 yrs | do not use

Other information

- each 30 mL contains:sodium 81 mg
- store at room temperature
- Do not refrigerate

Inactive ingredients

citric acid, D&C yellow #10, edetate disodium, FD&C blue #1, flavor, glycerin, propyl gallate, propylene glycol, purified water, sodium benzoate, sodium chloride, sodium citrate, sorbitol, sucralose

Questions or comments?

1-866-467-2748

Active ingredients (in each 30 mL) - Day Time

Acetaminophen 650 mg

Dextromethorphan HBr 20 mg

Guaifenesin 400 mg

Phenylephrine HCl 10 mg

Purpose

Pain reliever/fever reducer

Cough suppressant

Expectorant

Nasal decongestant

Uses

temporarily relieves common cold/flu symptoms:

- nasal congestion
- sinus congestion and pressure
- cough due to minor throat and bronchial irritation
- minor aches and pains
- headache
- fever
- sore throat
- reduces swelling of nasal passages
- temporarily restores freer breathing through the nose
- promotes nasal and/or sinus drainage
- helps loosen phlegm (mucus) and thin bronchial secretions to rid the bronchial passageways of bothersome mucus and make coughs more productive

Warnings

Liver warning:This product contains acetaminophen. Severe liver damage may occur if you take

- more than 4 doses in 24 hours, which is the maximum daily amount for this product.
- with other drugs containing acetaminophen
- 3 or more alcoholic drinks every day while using this product

Allergy alert:Acetaminophen may cause severe skin reactions. Symptoms may include:

- Skin reddening
- Blisters
- Rash

If a skin reaction occurs, stop use and seek medical help right away.

Sore throat warning:If sore throat is severe, persists for more than 2 days, is accompanied or followed by fever, headache, rash, nausea, or vomiting, consult a doctor promptly.

Do not use

- with any other drug containing acetaminophen (prescription or nonprescription). If you are not sure whether a drug contains acetaminophen, ask a doctor or pharmacist.
- if you are now taking a prescription monoamine oxidase inhibitor (MAOI) (certain drugs for depression, psychiatric, or emotional conditions, or Parkinson’s disease), or for 2 weeks after stopping the MAOI drug. If you do not know if your prescription drug contains an MAOI, ask a doctor or pharmacist before taking this product.

When using this product

do not use more than directed

Stop use and ask a doctor if

- you get nervous, dizzy or sleepless
- pain, nasal congestion, or cough gets worse or lasts more than 7 days
- fever gets worse or lasts more than 3 days
- redness or swelling is present
- new symptoms occur
- cough comes back or occurs with rash or headache that lasts. These could be signs of a serious condition.

If pregnant or breast-feeding,

ask a health professional before use.

Keep out of reach of children.

Overdose warning:In case of overdose, get medical help or contact a Poison Control Center right away at (1-800-222-1222). Quick medical attention is critical for adults as well as for children even if you do not notice any signs or symptoms.

Directions

- take only as directed
- only use the dose cup provided
- do not exceed 4 doses per 24 hrs

adults & children 12 yrs & over | 30 mL every 4 hrs
children 4 to under 12 yrs | ask a doctor
children under 4 yrs | do not use

Other information

- each 30 mL contains:sodium 81 mg
- store at room temperature.
- Do not refrigerate.

Inactive ingredients

citric acid, D&C yellow #10, edetate disodium,

FD&C blue #1, flavor, glycerin, propyl gallate, propylene glycol, purified water, sodium benzoate, sodium chloride, sodium citrate, sorbitol, sucralose

Package/Label Principal Display Panel

VALUE PACK

*Compare to the active ingredients in Vicks® Dayquil® Severe+ VapoCOOL™

DayTime

Cold & Flu

Relief

Acetaminophen- Pain reliever / Fever reducer

Dextromethorphan HBr - Cough supressant

Guaifenesin - Expectorant

Phenylephrine HCl - Nasal decongestant

For Relief of

- Minor Aches & Pains, Fever
- Nasal Congestion & Sinus Pressure
- Cough
- Chest Congestion

TWO BOTTLES, 12 FL OZ(354 mL)

**Compare to the active ingredients in Vicks® Nyquil® Severe+ VapoCOOL™

NightTime

Cold & Flu

Relief

Acetaminophen- Pain reliever / Fever reducer

Dextromethorphan HBr - Cough supressant

Doxylamine succinate - Antihistamine

Phenylephrine HCl - Nasal decongestant

For Relief of

- Minor Aches & Pains, Fever
- Nasal Congestion & Sinus Pressure
- Sneezing, Runny Nose
- Cough

Each; TOTAL 24 FL OZ(708 mL)